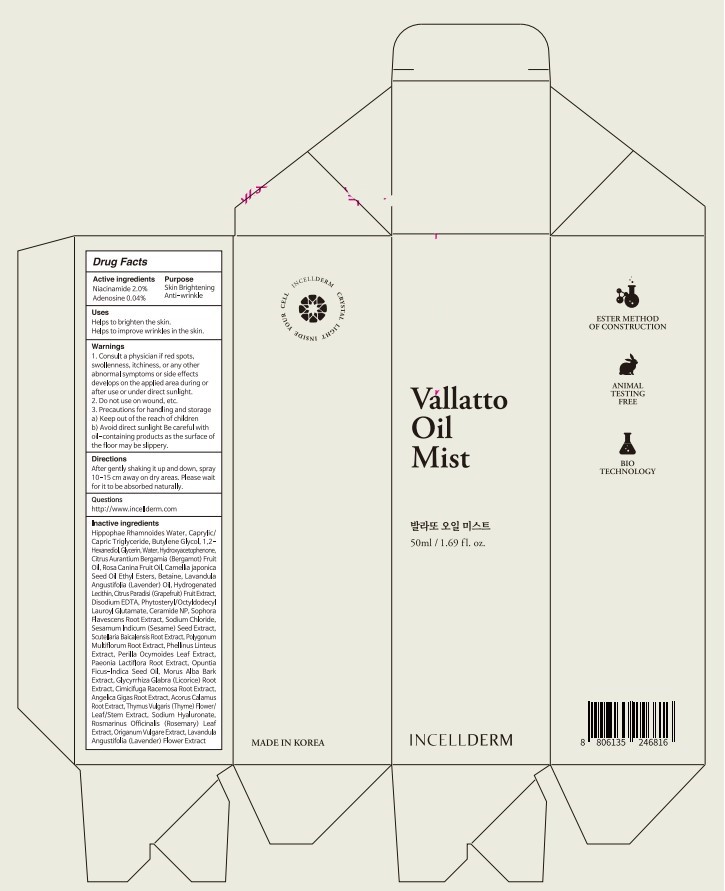 DRUG LABEL: INCELLDERM Vallatto Oi l Mist
NDC: 72650-040 | Form: SPRAY
Manufacturer: Riman Co., Ltd.
Category: otc | Type: HUMAN OTC DRUG LABEL
Date: 20201123

ACTIVE INGREDIENTS: Niacinamide 1.00 g/50 mL; Adenosine 0.02 g/50 mL
INACTIVE INGREDIENTS: HIPPOPHAE RHAMNOIDES FRUIT; MEDIUM-CHAIN TRIGLYCERIDES; Butylene Glycol

INCELLDERM Vallatto Oil Mist

ACTIVE INGREDIENTS

Niacinamide 2.0%

Adenosine 0.04%

INACTIVE INGREDIENTS

Hippophae Rhamnoides Water, Caprylic/Capric Triglyceride, Butylene Glycol, 1,2-Hexanediol, Glycerin, Water, Hydroxyacetophenone, Citrus Aurantium Bergamia (Bergamot) Fruit Oil, Rosa Canina Fruit Oil, Camellia japonica Seed Oil Ethyl Esters, Betaine, Lavandula Angustifolia (Lavender) Oil, Hydrogenated Lecithin, Citrus Paradisi (Grapefruit) Fruit Extract, Disodium EDTA, Phytosteryl/Octyldodecyl Lauroyl Glutamate, Ceramide NP, Sophora Flavescens Root Extract, Sodium Chloride, Sesamum Indicum (Sesame) Seed Extract, Scutellaria Baicalensis Root Extract, Polygonum Multiflorum Root Extract, Phellinus Linteus Extract, Perilla Ocymoides Leaf Extract, Paeonia Lactiflora Root Extract, Opuntia Ficus-Indica Seed Oil, Morus Alba Bark Extract, Glycyrrhiza Glabra (Licorice) Root Extract, Cimicifuga Racemosa Root Extract, Angelica Gigas Root Extract, Acorus Calamus Root Extract, Thymus Vulgaris (Thyme) Flower/Leaf/Stem Extract, Sodium Hyaluronate, Rosmarinus Officinalis (Rosemary) Leaf Extract, Origanum Vulgare Extract, Lavandula Angustifolia (Lavender) Flower Extract

PURPOSE

Skin Brightening

Anti-wrinkle

WARNINGS

1. Consult a physician if red spots, swollenness, itchiness, or any other abnormal symptoms or side effects develops on the applied area during or after use or under direct sunlight.
2. Do not use on wound, etc.
3. Precautions for handling and storage
a) Keep out of the reach of children
b) Avoid direct sunlight Be careful with oil-containing products as the surface of the floor may be slippery.

KEEP OUT OF REACH OF CHILDREN

Uses

Helps to brighten the skin.
Helps to improve wrinkles in the skin.

Directions

After gently shaking it up and down, spray 10-15 cm away on dry areas. Please wait for it to be absorbed naturally.

QUESTIONS

http://www.incellderm.com